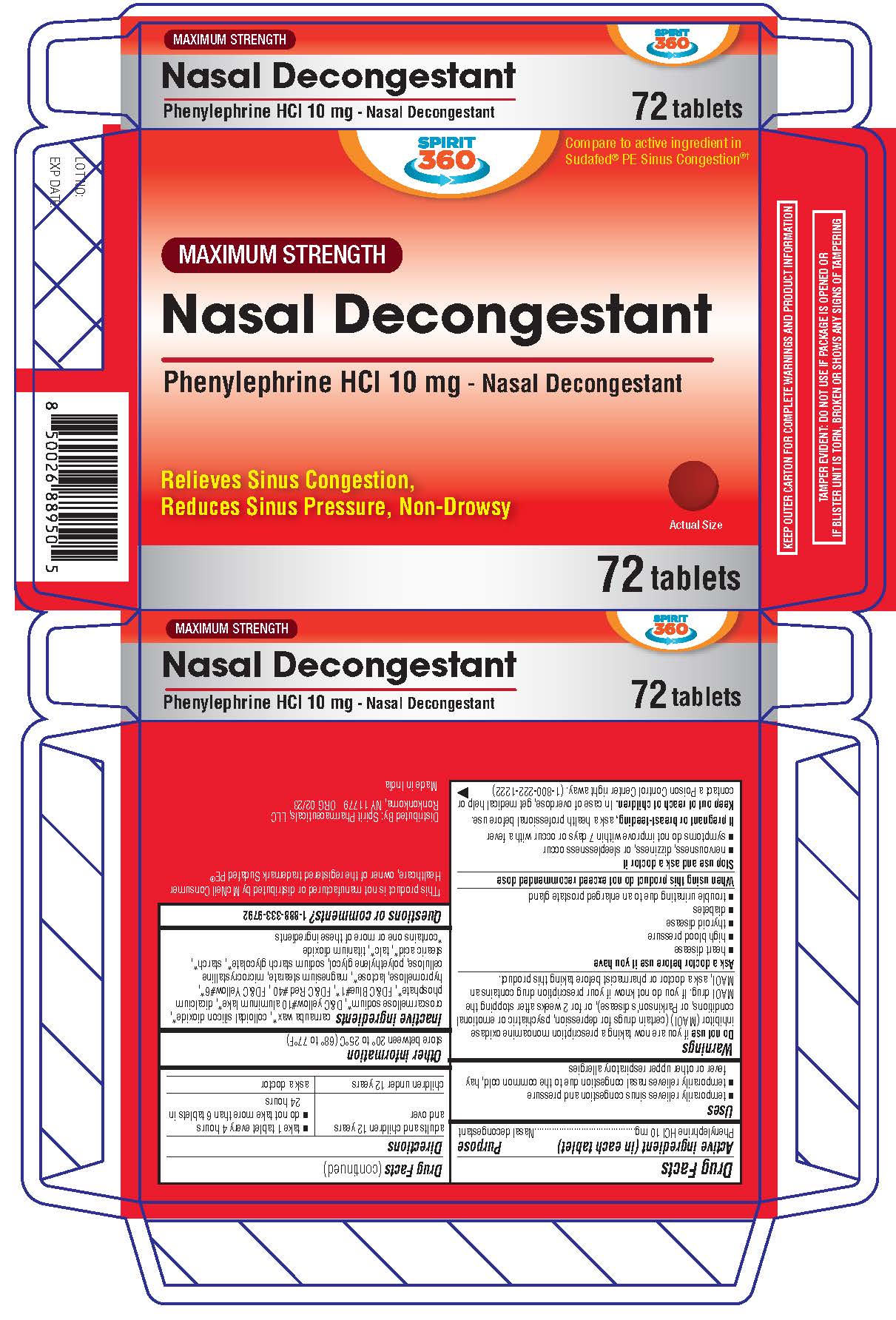 DRUG LABEL: Maximum Strength Nasal Decongestant
NDC: 68210-5011 | Form: TABLET, COATED
Manufacturer: Spirit Pharmaceuticals LLC
Category: otc | Type: HUMAN OTC DRUG LABEL
Date: 20241213

ACTIVE INGREDIENTS: PHENYLEPHRINE HYDROCHLORIDE 10 mg/1 1
INACTIVE INGREDIENTS: CARNAUBA WAX; SILICON DIOXIDE; CROSCARMELLOSE SODIUM; D&C YELLOW NO. 10 ALUMINUM LAKE; CALCIUM PHOSPHATE; FD&C BLUE NO. 1; FD&C RED NO. 40; FD&C YELLOW NO. 6; HYPROMELLOSES; LACTOSE MONOHYDRATE; MAGNESIUM STEARATE; MICROCRYSTALLINE CELLULOSE; POLYETHYLENE GLYCOL, UNSPECIFIED; SODIUM STARCH GLYCOLATE TYPE A; STARCH, POTATO; STEARIC ACID; TALC; TITANIUM DIOXIDE

Maximum Strength Nasal Decongestant

Active Ingredient (in each tablet)

Phenylephrine Hydrochloride 10 mg

Purpose

Nasal decongestant

Uses

• temporarily relieves sinus congestion and pressure • temporarily relieves nasal congestion due to the common cold, hay fever or other upper respiratory allergies

Warnings

Do not use if you are now taking a prescription monoamine oxidase inhibitor (MAOI) (certain drugs for depression, psychiatric, or emotional conditions, or Parkinson’s disease), or for 2 weeks after stopping the MAOI drug. If you do not know if your prescription drug contains an MAOI, ask a doctor or pharmacist before taking this product.

Ask a doctor before use if you have • heart disease • high blood pressure • thyroid disease • diabetes • trouble urinating due to an enlarged prostate gland

When using this product do not exceed recommended dose

Stop use and ask a doctor if • nervousness, dizziness, or sleeplessness occur • symptoms do not improve within 7 days or occur with a fever

PREGNANCY OR BREAST FEEDING

If pregnant or breast-feeding, ask a health professional before use.

Keep out of reach of children. In case of overdose, get medical help or contact a Poison Control Center right away. (1-800-222-1222)

Directions

adults & children12 years & over | • take 1 tablet every 4 hours; • do not take more than 6 tablets in 24 hours
children under 12 years | ask a doctor

Other information

• store between 20-25°C (68-77°F)

Inactive ingredients

Carnauba wax*, colloidal silicon dioxide*, croscarmellose sodium*, D&C yellow#10 aluminum lake*, dicalcium phosphate*, FD&C Blue#1*, FD&C Red #40 , FD&C Yellow#6*, hypromellose, lactose*, magnesium stearate, microcrystalline cellulose, polyethylene glycol, sodium starch glycolate*, starch*, stearic acid*, talc*, *contains one or more of these ingredients

Questions or comments?

1-888-333-9792

Distributed By:
Spirit Pharmaceuticals, LLC
Ronkonkoma, NY 11779

Made in India